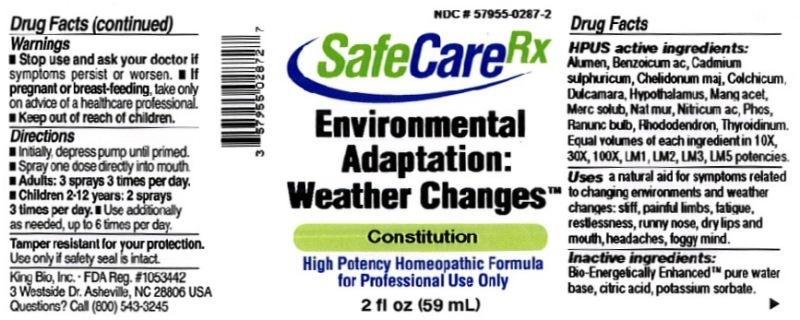 DRUG LABEL: Environmental Adaptation Weather Changes
NDC: 57955-0287 | Form: LIQUID
Manufacturer: King Bio Inc.
Category: homeopathic | Type: HUMAN OTC DRUG LABEL
Date: 20150819

ACTIVE INGREDIENTS: POTASSIUM ALUM 10 [hp_X]/59 mL; BENZOIC ACID 10 [hp_X]/59 mL; CADMIUM SULFATE 10 [hp_X]/59 mL; CHELIDONIUM MAJUS 10 [hp_X]/59 mL; COLCHICUM AUTUMNALE BULB 10 [hp_X]/59 mL; SOLANUM DULCAMARA TOP 10 [hp_X]/59 mL; BOS TAURUS HYPOTHALAMUS 10 [hp_X]/59 mL; MANGANESE ACETATE TETRAHYDRATE 10 [hp_X]/59 mL; MERCURIUS SOLUBILIS 10 [hp_X]/59 mL; SODIUM CHLORIDE 10 [hp_X]/59 mL; NITRIC ACID 10 [hp_X]/59 mL; PHOSPHORUS 10 [hp_X]/59 mL; RANUNCULUS BULBOSUS 10 [hp_X]/59 mL; RHODODENDRON AUREUM LEAF 10 [hp_X]/59 mL; THYROID, UNSPECIFIED 10 [hp_X]/59 mL
INACTIVE INGREDIENTS: WATER; ANHYDROUS CITRIC ACID; POTASSIUM SORBATE

Environmental Adaptation Weather Changes

Drug Facts

____________________________________________________________________________________________________________________

HPUS active ingredients: Alumen, Benzoicum acidum, Cadmium sulphuricum, Chelidonium majus, Colchicum autumnale, Dulcamara, Hypothalamus, Manganum aceticum, Mercurius solubilis, Natrum muriaticum, Nitricum acidum, Phosphorus, Ranunculus bulbosus, Rhododendron chrysanthum, Thyroidinum. Equal volumes of each ingredient in 10X, 30X, 100X, LM1, LM2, LM3, LM5 potencies.

INDICATIONS AND USAGE

Uses a natural aid for symptoms related to changing environments and weather changes: stiff, painful limbs, fatigue, restlessness, runny nose, dry lips and mouth, headaches, foggy mind.

INACTIVE INGREDIENT

Inactive ingredients: Bio-Energetically Enhanced pure water, citric acid, potassium sorbate.

Warnings

- Stop use and ask your doctor if symptoms persist or worsen.
- If pregnant or breast-feeding, take only on advice of a healthcare professional.

- Keep out of reach of children.

Directions:

- Initially, depress pump until primed.
- Spray one dose directly into mouth.
- Adults: 3 sprays 3 times per day.
- Children 2-12 years: 2 sprays 3 times per day.
- Use additionally as needed, up to 6 times per day.

OTHER SAFETY INFORMATION

Tamper resistant for your protection. Use only if safety seal is intact.

PURPOSE

Uses a natural aid for symptoms related to changing environments and weather changes:

- stiff, painful limbs
- fatigue
- restlessness
- runny nose
- dry lips and mouth
- headaches
- foggy mind